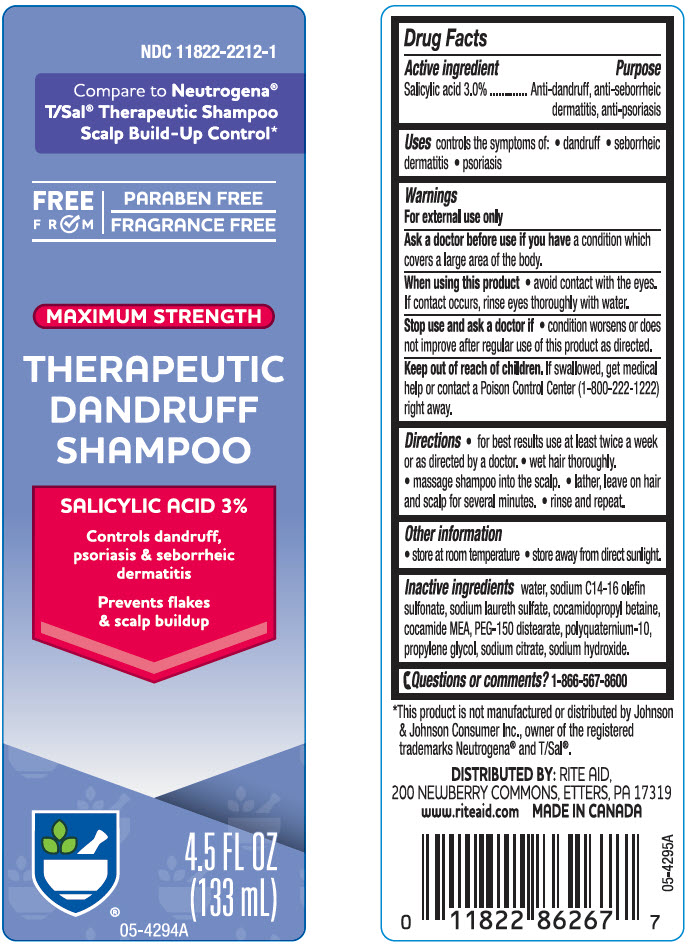 DRUG LABEL: MAXIMUM STRENGTH THERAPEUTIC DANDRUFF 
NDC: 11822-2212 | Form: SHAMPOO
Manufacturer: Rite Aid
Category: otc | Type: HUMAN OTC DRUG LABEL
Date: 20240307

ACTIVE INGREDIENTS: Salicylic acid 30 mg/1 mL
INACTIVE INGREDIENTS: Water; Sodium C14-16 Olefin Sulfonate; Sodium Laureth-3 Sulfate; Cocamidopropyl Betaine; Coco Monoethanolamide; PEG-150 Distearate; POLYQUATERNIUM-10 (30000 MPA.S AT 2%); Propylene Glycol; Sodium Citrate, Unspecified Form; Sodium Hydroxide

MAXIMUM STRENGTH THERAPEUTIC DANDRUFF SHAMPOO
Anti-dandruff, anti-seborrheic dermatitis, anti-psoriasis

Drug Facts

Active ingredient

Salicylic acid 3.0%

Purpose

Anti-dandruff, anti-seborrheic dermatitis, anti-psoriasis

Uses

controls the symptom of:

- dandruff
- seborrheic dermatitis
- psoriasis

Warnings

For external use only.

Ask a doctor before use if you have a condition that covers a large area of the body.

When using this product

⬥ avoid contact with the eyes. If contact occurs, rinse eyes thoroughly with water.

Stop use and ask a doctor if

⬥ condition worsens or does not improve after regular use of this product as directed.

Keep out of reach of children. If swallowed, get medical help or contact a Poison Control Center (1-800-222-1222) right away.

Directions

⬥ for best results use at least twice a week or as directed by a doctor.
⬥ wet hair thoroughly.
⬥ massage shampoo into the scalp.
⬥ lather, leave on hair and scalp for several minutes.
⬥ rinse and repeat.

Other information

- store at room temperature
- store away from direct sunlight

Inactive ingredients

water, sodium C14-16 olefin sulfonate, sodium laureth sulfate, cocamidopropyl betaine, cocamide MEA, PEG-150 distearate, polyquaternium-10, propylene glycol, sodium citrate, sodium hydroxide

Questions or comments?

1-866-567-8600

DISTRIBUTED BY: RITE AID,
200 NEWBERRY COMMONS, ETTERS, PA 17319

PRINCIPAL DISPLAY PANEL - 133 mL Bottle Label

NDC 11822-2212-1

Compare to Neutrogena®
T/Sal® Therapeutic Shampoo
Scalp Build-Up Control*

FREE
FROM
PARABEN FREE
FRAGRANCE FREE

MAXIMUM STRENGTH

THERAPEUTIC
DANDRUFF
SHAMPOO

SALICYLIC ACID 3%

Controls dandruff,
psoriasis & seborrheic
dermatitis

Prevents flakes
& scalp buildup

4.5 FL OZ
(133 mL)

05-4294A